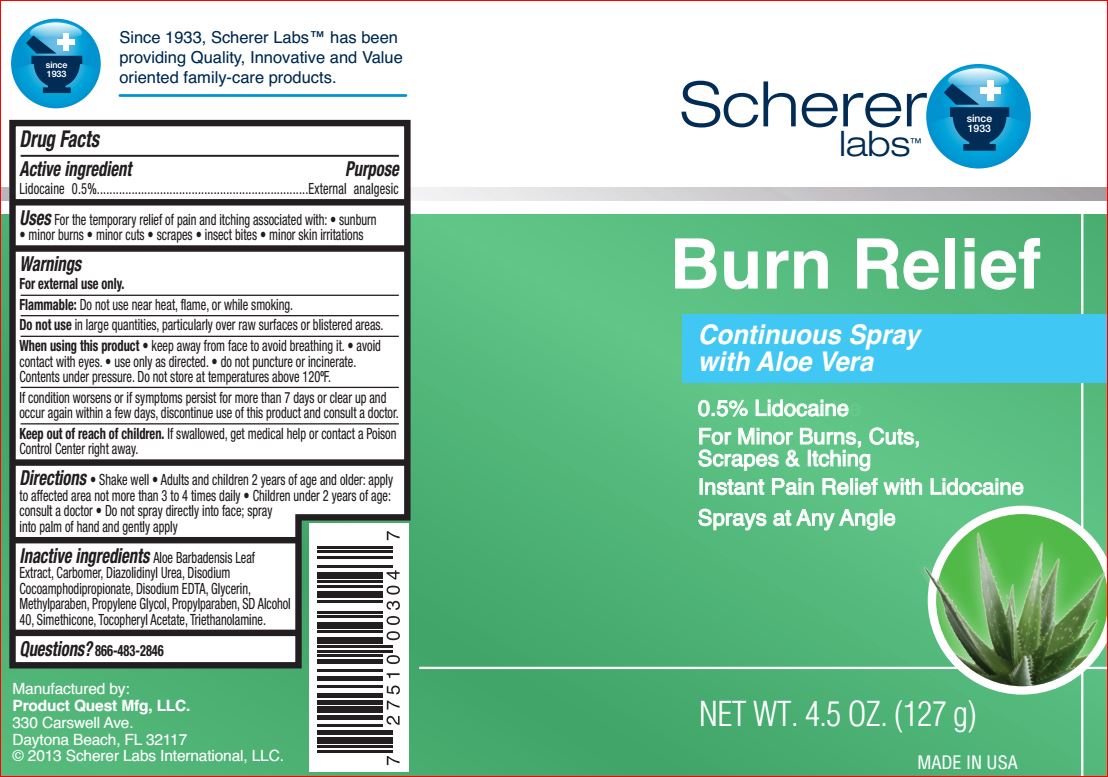 DRUG LABEL: Burn Relief
NDC: 64048-5115 | Form: spray
Manufacturer: Product Quest Mfg
Category: otc | Type: HUMAN OTC DRUG LABEL
Date: 20180723

ACTIVE INGREDIENTS: Lidocaine 0.5 g/100 g
INACTIVE INGREDIENTS: ALOE VERA LEAF; Diazolidinyl Urea; Disodium Cocoamphodipropionate; EDETATE DISODIUM; Glycerin; Methylparaben; Propylene Glycol; Propylparaben; ALCOHOL; .ALPHA.-TOCOPHEROL ACETATE; TROLAMINE

Drug Facts

Active ingredient Purpose

Lidocaine 0.5% External analgesic

Uses

Temporarily relieves pain and itching due to

• sunburn • minor burns • minor cuts • scrapes

• insect bites • minor skin irritation

Warnings

For external use only

When using this product

- keep out of your eyes
- use only as directed
- do not puncture or incinerate. Contents under pressure. Do not store at temperature above 120F.

Stop use and ask a doctor if

- condition gets worse
- symptoms last more than 7 days
- symptoms clear up and occur again within a few days

Keep out of reach of the children

If swallowed, get medical help or contact a Poison Control Center right away

Directions

• shake well
• adults and children 2 years of age and older: apply to affected area, not more than 3 to 4 times daily
• children under 2 years of age: ask a doctor

• to apply to face, spray into palm of hand and gently apply

Inactive ingredients

Aloe Barbadensis Leaf Juice, Carbomer, Diazolidinyl Urea, Disodium Cocoamphodipropionate, Disodium EDTA, Glycerin, Methylparaben, Propylene Glycol, Propylparaben, SD Alcohol 40, Simethicone, Tocopheryl Acetate, Triethanolamine

Questions and comments?

1-866-483-2846